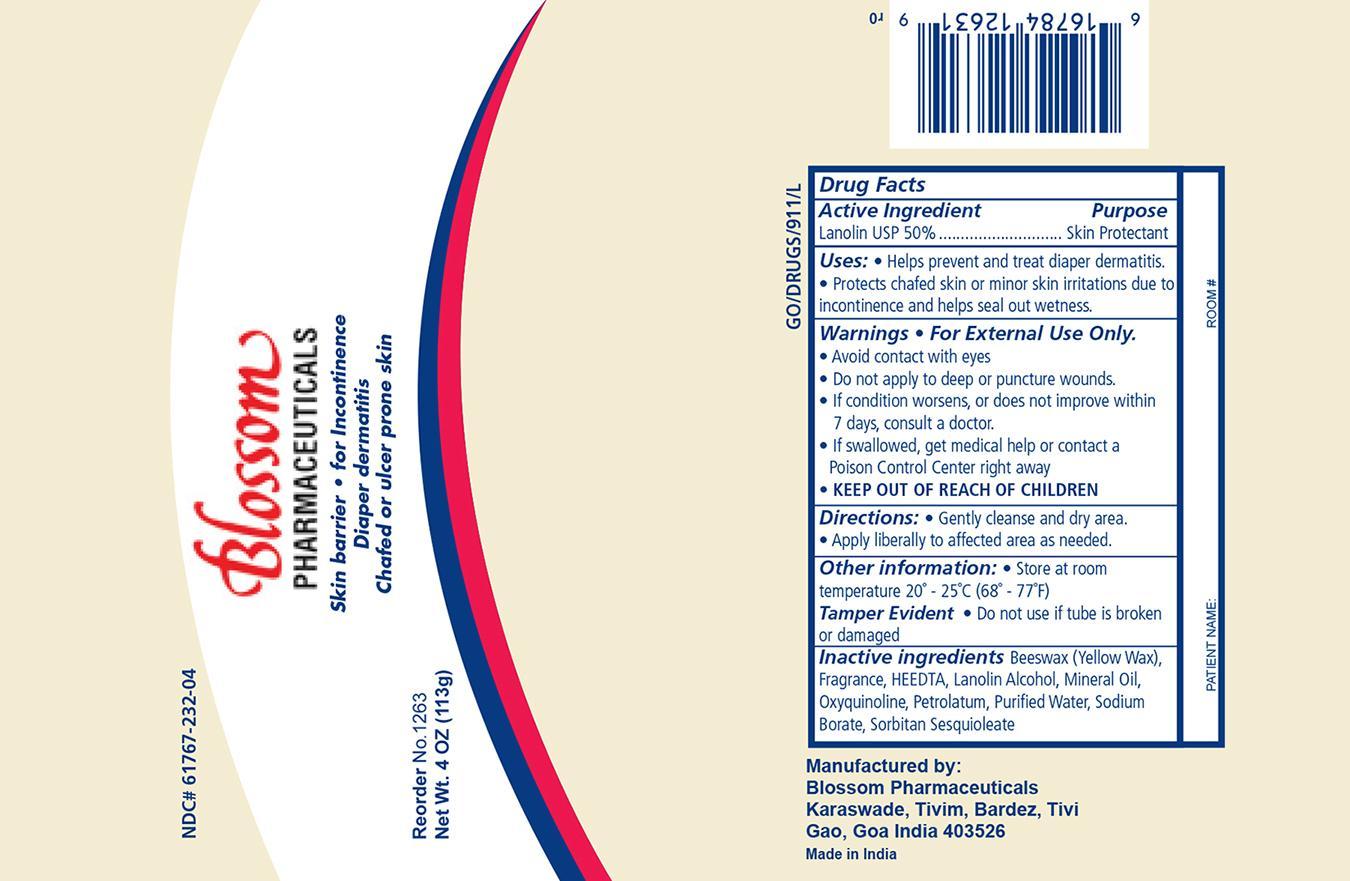 DRUG LABEL: Lana1263
NDC: 61767-232 | Form: OINTMENT
Manufacturer: Blossom Pharmaceuticals
Category: otc | Type: HUMAN OTC DRUG LABEL
Date: 20141023

ACTIVE INGREDIENTS: LANOLIN 50 g/100 g
INACTIVE INGREDIENTS: WHITE WAX; LANOLIN ALCOHOLS; MINERAL OIL; SODIUM BORATE; WATER; EDETIC ACID; PETROLATUM

Lanashield Ointment

ACTIVE INGREDIENT

Active ingredient Purpose
Lanolin USP 50% Skin Protectant

Purpose:

- Helps prevent and treat diaper dermatitis
- Protects chafed skin or minor skin irritations due to incontinence and helps seal out wetness

Warnings

For External Use Only

Keep Out Of Reach Of Children

- If swallowed, get medical help or contact a Poison Control Center right away

Indications & Usage

- Avoid contact with eyes
- Do not apply to deep or puncture wounds
- If condition worsens, or does not improve within 7 days, consult a doctor

Dosage & Administration

- Gently cleanse and dry area
- Apply liberally to affected area as needed

Other information:

- Store at room temperature 20 deg C to 25 deg C 68 deg F to 77 deg F

Inactive Ingredients

Beeswax (White), EDTA, Emulsifying wax, Lanolin alcohol, Lavender perfume, Mineral oil, Petrolatum, Purified water, Sodium borate

Principal Display Panel

Lana1263 Ointment

Lana1263.jpg